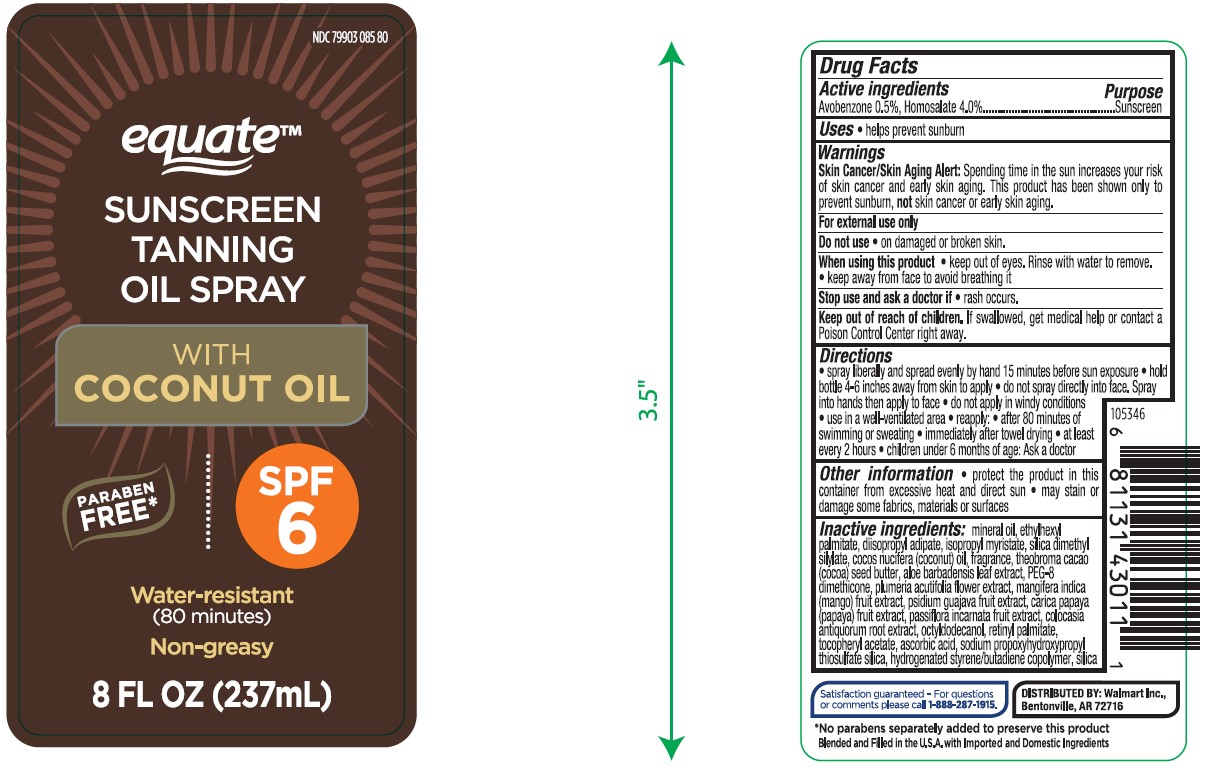 DRUG LABEL: Equate Sunscreen Tanning Oil With Coconut Oil SPF 6
NDC: 79903-085 | Form: SPRAY
Manufacturer: WAL-MART STORES INC.
Category: otc | Type: HUMAN OTC DRUG LABEL
Date: 20241023

ACTIVE INGREDIENTS: AVOBENZONE 5 mg/1 mL; HOMOSALATE 40 mg/1 mL
INACTIVE INGREDIENTS: MINERAL OIL; DIISOPROPYL ADIPATE; COCONUT OIL; ALOE VERA LEAF; GUAVA; ISOPROPYL MYRISTATE; PLUMERIA RUBRA FLOWER; PEG-8 DIMETHICONE; PAPAYA; MANGO; PASSIFLORA INCARNATA FRUIT; OCTYLDODECANOL; .ALPHA.-TOCOPHEROL ACETATE, DL-; ASCORBIC ACID; SILICON DIOXIDE; SILICA DIMETHYL SILYLATE; VITAMIN A PALMITATE; ETHYLHEXYL PALMITATE; SODIUM PROPOXYHYDROXYPROPYL THIOSULFATE SILICA; COCOA BUTTER; COLOCASIA ESCULENTA ROOT; LIGHT MINERAL OIL

Equate Sunscreen Tanning Oil Spray With Coconut Oil SPF 6

Active ingredients

Avobenzone 0.5%, Homosalate 4.0%

Purpose

Sunscreen

Uses

• helps prevent sunburn

Warnings

Skin Cancer/Skin Aging Alert: Spending time in the sun increases your risk of skin cancer and early signs of aging. This product has been shown only to prevent sunburn, not skin cancer or early skin aging.

For external use only

Do not use

• on damaged or broken skin.

When using this product

• keep out of eyes. Rinse with water to remove. • Keep away from face to avoid breathing it.

Stop use and Ask a doctor if

• rash occurs.

Keep out of reach of children.

If swallowed, get medical help or contact a Poison Control Center right away.

Directions

• Spray liberally and spread evenly by hand 15 minutes before sun exposure
• Hold can 4-6 inches away from the skin to apply
• Do not spray directly into face. Spray into hands then apply to face
• Do not apply in windy conditions
• Use in a well-ventilated area

• reapply:
• after 80 minutes of swimming or sweating
• immediately after towel drying
• at least every 2 hours
• children under 6 months of age: Ask a doctor

Other information

• protect the product in this container from excessive heat and direct sun
• may stain or damage some fabrics, materials or surfaces

Inactive ingredients

Mineral Oil, Ethylhexyl Palmitate, Diisopropyl Adipate, Isopropyl Myristate, Silica Dimethyl Silylate, Cocos Nucifera (Coconut) Oil, Fragrance, Theobroma Cacao (Cocoa) Seed Butter, Aloe Barbadensis Leaf Extract, PEG-8 Dimethicone, Plumeria Acutifolia Flower Extract, Mangifera Indica (Mango) Fruit Extract, Psidium Guajava Fruit Extract, Carica Papaya (Papaya) Fruit Extract, Passiflora Incarnata Fruit Extract, Colocasia Antiquorum Root Extract, Octyldodecanol, Retinyl Palmitate, Tocopheryl Acetate, Ascorbic Acid, Sodium Propoxyhydroxypropyl Thiosulfate Silica, Hydrogenated Styrene/Butadiene Copolymer, Silica